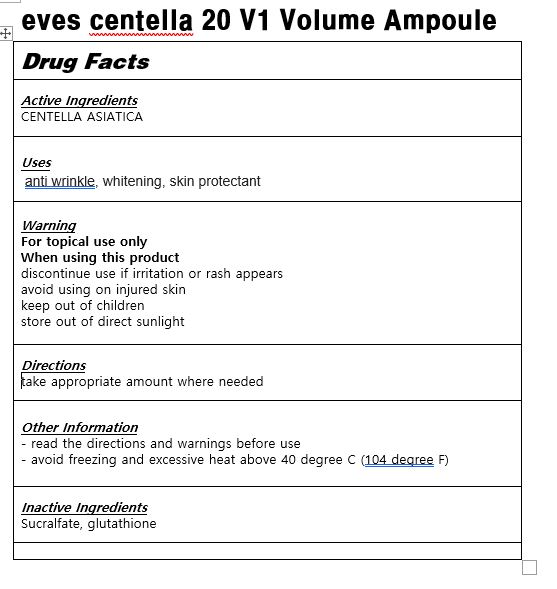 DRUG LABEL: eves centella 20 V1 Volume Ampoule
NDC: 83113-0001 | Form: LIQUID
Manufacturer: eveskorea
Category: otc | Type: HUMAN OTC DRUG LABEL
Date: 20221121

ACTIVE INGREDIENTS: CENTELLA ASIATICA 1 g/100 mL
INACTIVE INGREDIENTS: SUCRALFATE; GLUTATHIONE

Drug Facts

ACTIVE INGREDIENT

CENTELLA ASIATICA

PURPOSE

anti wrinkle, whitening

KEEP OUT OF REACH OF THE CHILDREN

INDICATIONS AND USAGE

take proper amount where needed

Keep out of reach of children.

Irritation around the eyes, ears, mucous membranes, including the mouth, under the skin irritation and rashes

Store in the room temperature

DOSAGE AND ADMINISTRATION

for oral use only

INACTIVE INGREDIENT

sucralfate, glutathione,